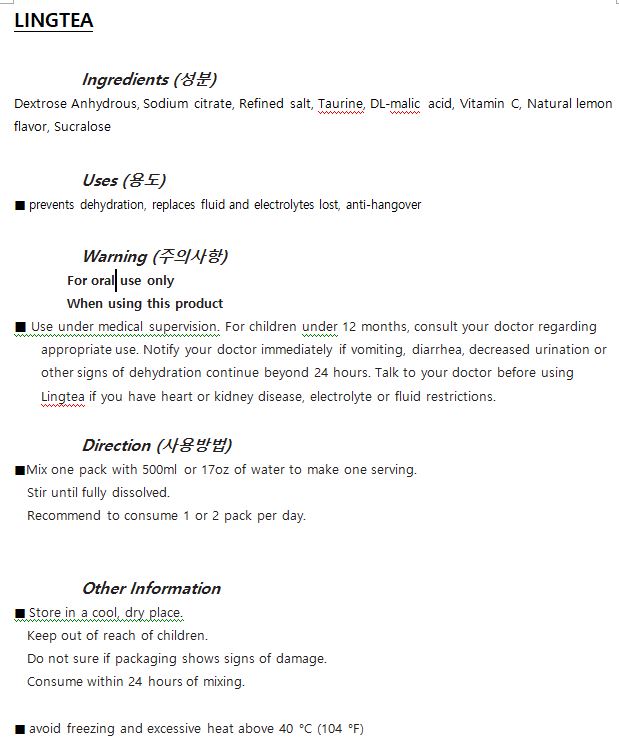 DRUG LABEL: LINGTEA
NDC: 72355-0002 | Form: POWDER, FOR SOLUTION
Manufacturer: LINGER WATER
Category: otc | Type: HUMAN OTC DRUG LABEL
Date: 20180627

ACTIVE INGREDIENTS: ANHYDROUS DEXTROSE 5 g/100 g
INACTIVE INGREDIENTS: SUCRALOSE; SODIUM CITRATE

ACTIVE INGREDIENT

Dextrose Anhydrous

INACTIVE INGREDIENT

Sodium citrate, Refined salt, DL-malic acid, Vitamin C, Natural lemon flavor, Sucralose

PURPOSE

prevents dehydration, replaces fluid and electrolytes lost, anti-hangover

keep out or reach of the children

INDICATIONS AND USAGE

Mix one pack with 500ml or 17oz of water to make one serving.

Stir until fully dissolved.

Recommend to consume 1 or 2 pack per day.

WARNINGS

Use under medical supervision.

For children under 12 months, consult your doctor regarding appropriate use.

Notify your doctor immediately if vomiting, diarrhea, decreased urination or other signs of dehydration continue beyond 24 hours.

Talk to your doctor before using Lingtea if you have heart or kidney disease, electrolyte or fluid restrictions

DOSAGE AND ADMINISTRATION

for oral use only